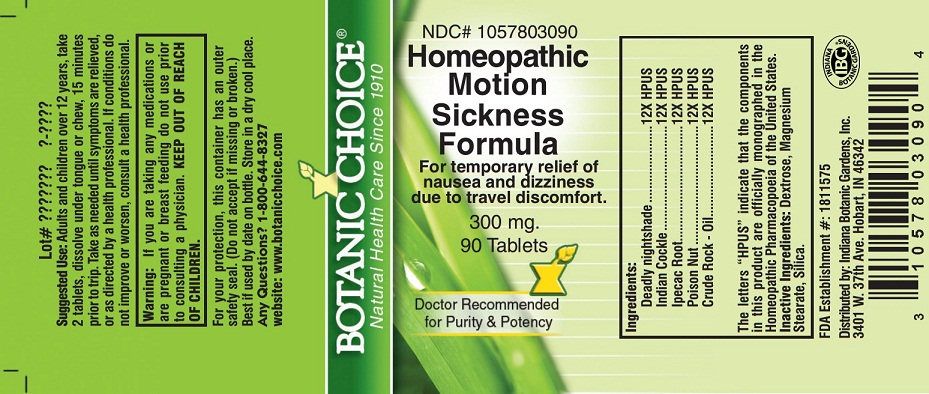 DRUG LABEL: Homeopathic Motion Sickness
NDC: 10578-030 | Form: TABLET
Manufacturer: Indiana Botanic Gardens
Category: homeopathic | Type: HUMAN OTC DRUG LABEL
Date: 20130401

ACTIVE INGREDIENTS: ATROPA BELLADONNA 12 [hp_X]/1 1; ANAMIRTA COCCULUS SEED 12 [hp_X]/1 1; IPECAC 12 [hp_X]/1 1; STRYCHNOS NUX-VOMICA SEED 12 [hp_X]/1 1; LIQUID PETROLEUM 12 [hp_X]/1 1
INACTIVE INGREDIENTS: DEXTROSE; MAGNESIUM STEARATE; SILICON DIOXIDE

Homeopathic Motion Sickness

Suggested Use:

Adults and children over 12 years, take 2 tablets, dissolve under tongue or chew, 15 minutes prior to trip. Take as needed until symptoms are relieved, or as directed by a health professional.

STOP USE

If conditions do not improve or worsen, consult a health professional.

Warning:

If you are taking any medications or are pregnant or breast feeding do not use prior to consulting a physician.

KEEP OUT OF REACH OF CHILDREN.

For your protection, this container has an outer safety seal. (Do not accept if missing or broken.) Best if used by date on bottle. Store in a dry cool place.

Any Questions?

Any Questions? 1-800-644-8327

website: www.botanicchoice.com

PURPOSE

INDICATIONS AND USAGE

For temporary relief of nausea and dizziness due to travel discomfort.

Ingredients:

Deadly nightshade ......................12X HPUS

Indian Cockle ..............................12X HPUS

Ipecac Root .................................12X HPUS

Poison Nut ..................................12X HPUS

Crude Rock - Oil ..........................12X HPUS

The letters “HPUS” indicate that the components in this product are officially monographed in the Homeopathic Pharmacopoeia of the United States.

Inactive Ingredients:

Dextrose, Magnesium Stearate, Silica.

FDA Establishment #: 1811575

Distributed by: Indiana Botanic Gardens, Inc.

3401 W. 37th Ave. Hobart, IN 46342

Botanic Choice®

Natural Health Care Since 1910

NDC# 1057803090

Homeopathic Motion Sickness Formula

For temporary relief of nausea and dizziness due to travel discomfort.

300 mg.

90 Tablets

Doctor Recommended for Purity & Potency